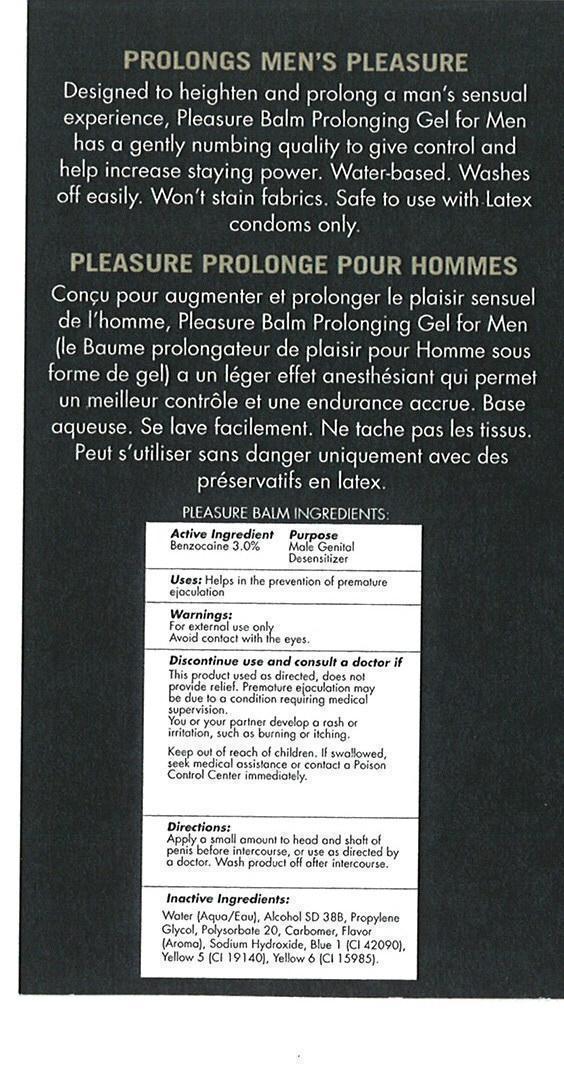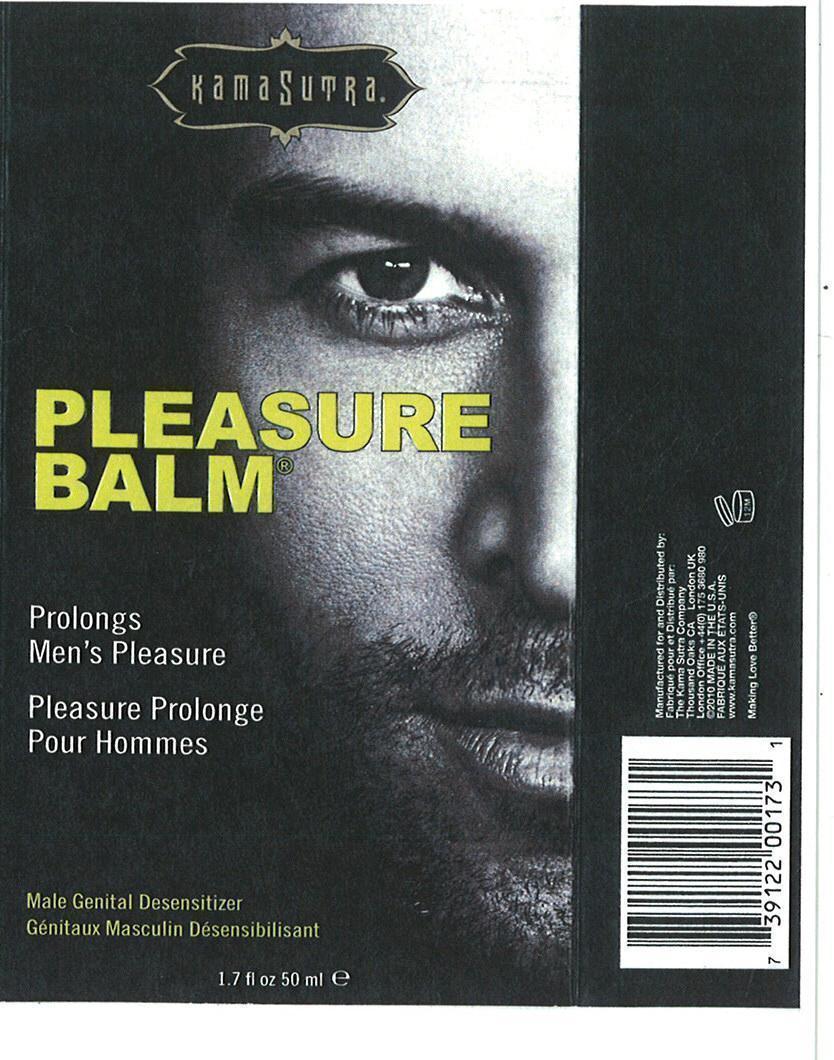 DRUG LABEL: Male Desensitizer
NDC: 75956-145 | Form: GEL
Manufacturer: Kama Sutra
Category: otc | Type: HUMAN OTC DRUG LABEL
Date: 20140731

ACTIVE INGREDIENTS: BENZOCAINE 3.00 g/100 mL
INACTIVE INGREDIENTS: WATER; PROPYLENE GLYCOL; POLYSORBATE 20; SODIUM HYDROXIDE; FD&C BLUE NO. 1; FD&C YELLOW NO. 5; FD&C YELLOW NO. 6

Pleasure Balm

Active Ingredients Purpose

Benzocaine 3.0% Male genital Desensitizer

PURPOSE

Uses: Helps in the prevention of premature ejaculation

Keep out of reach of children. If swallowed, seek medical assistance or contact a Poison Control Center

INDICATIONS AND USAGE

Discontinue use and consult a doctor if

This product used as directed, does not provide relief. Premature ejaculation may be due to a condition requiring medical supervision.

You or your partner develop a rash or irritation, such as burning or itching.

Warnings

For external use only

Avoid contact with the eyes.

DIrections

Apply a small amount to head and shaft of penis before intercourse, or use as directed by a doctor. Wash product off after intercourse.

Inactive ingredients:

Water (Aqua/Eau), Alcohol SD 38B, Propylene Glycol, Polysorbate 20, Carbomer, flavor (Aroma), Sodium Hydroxide, Blue 1 (CI 42090), Yellow 5 (CI 19140), Yellow 6 (CI 15985)

PACKAGE LABEL

Kama Sutra

Pleasure Balm

Male Genital Desensitizer
1.7 fl. oz. 50ml